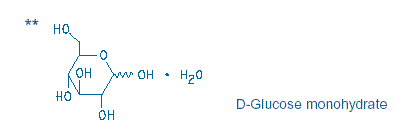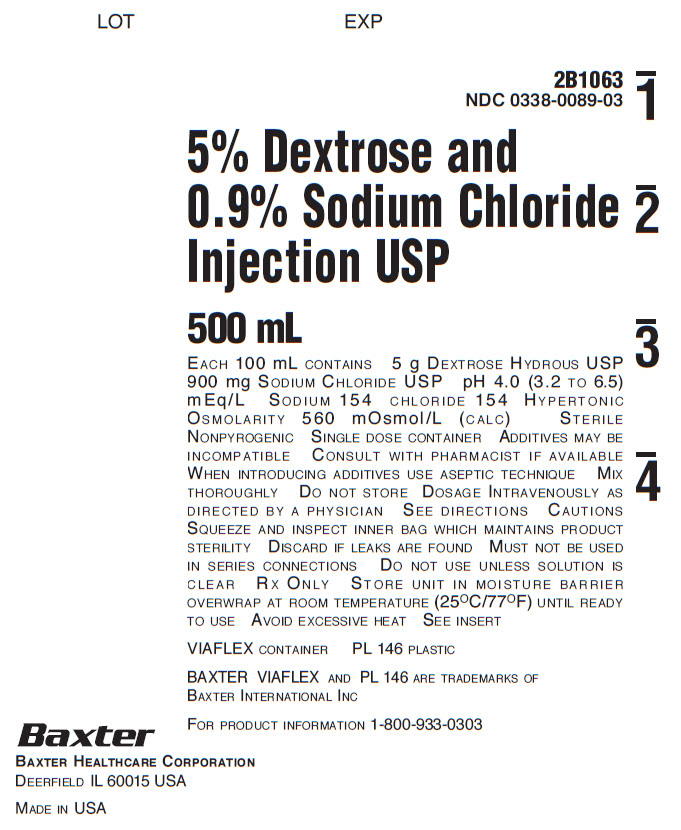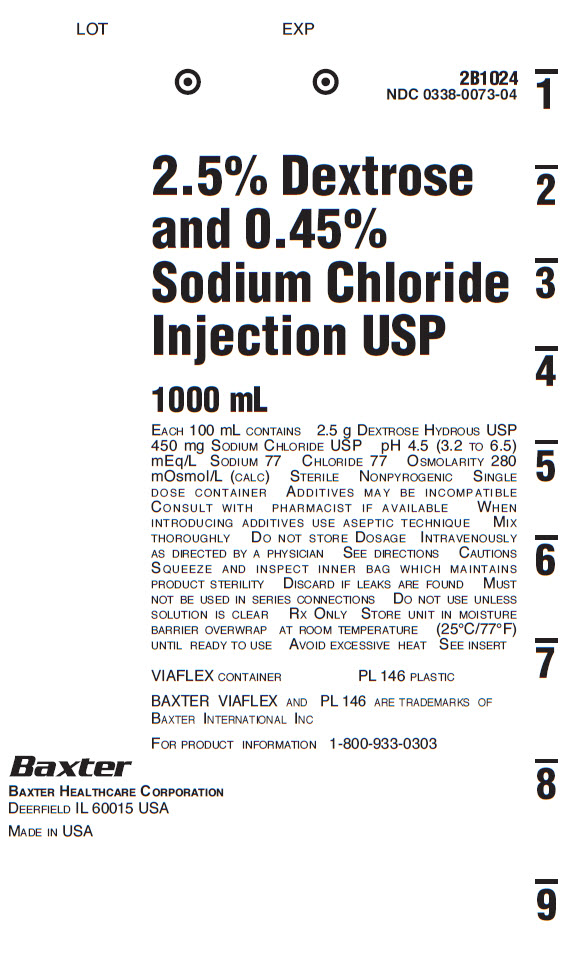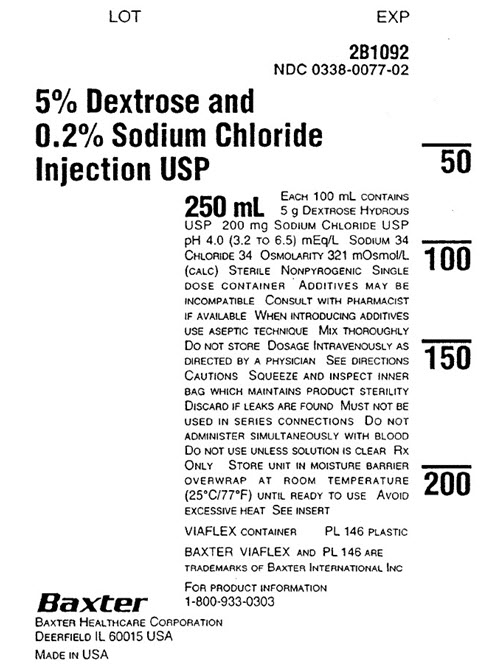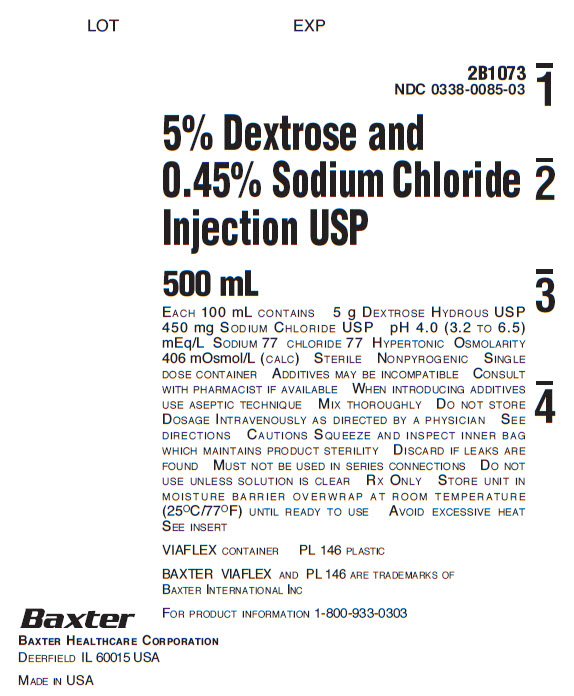 DRUG LABEL: Dextrose and Sodium Chloride
NDC: 0338-0073 | Form: INJECTION, SOLUTION
Manufacturer: Baxter Healthcare Company
Category: prescription | Type: HUMAN PRESCRIPTION DRUG LABEL
Date: 20250826

ACTIVE INGREDIENTS: DEXTROSE MONOHYDRATE 2.5 g/100 mL; SODIUM CHLORIDE 450 mg/100 mL
INACTIVE INGREDIENTS: WATER

HIGHLIGHTS OF PRESCRIBING INFORMATION

These highlights do not include all the information needed to use DEXTROSE AND SODIUM CHLORIDE INJECTION safely and effectively. See full prescribing information for DEXTROSE AND SODIUM CHLORIDE INJECTION.
DEXTROSE AND SODIUM CHLORIDE injection, for intravenous use
Initial U.S. Approval: 1970

RECENT MAJOR CHANGES

Contraindications (4) 08/2019

Warnings and Precautions (5.1, 5.2, 5.3, 5.4, 5.5, 5.6, 5.7) 08/2019

1 INDICATIONS AND USAGE

Dextrose and Sodium Chloride Injection is indicated as a source of water, electrolytes and calories. (1)

2 DOSAGE AND ADMINISTRATION

- Only for intravenous infusion. (2.1)
- See full prescribing information for information on preparation, administration, dosing considerations and instructions for use. (2.1, 2.2, 2.3)

3 DOSAGE FORMS AND STRENGTHS

Dextrose and Sodium Chloride Injection is available in multiple strengths. See full prescribing information for detailed description of each product. (3)

4 CONTRAINDICATIONS

- Known hypersensitivity to dextrose, or sodium chloride (4, 5.1)
- Clinically significant hyperglycemia (4, 5.2)

5 WARNINGS AND PRECAUTIONS

- Hypersensitivity Reactions: Monitor for signs and symptoms and discontinue infusion if reactions occur. (5.1)
- Hyperglycemia or Hyperosmolar Hyperglycemic State: Monitor blood glucose and administer insulin as needed. (5.2, 8.4)
- Hyponatremia, Hypokalemia, Hypernatremia and Hyperchloremia: Avoid in patients with or at risk for hypo-/hypernatremia and hypokalemia. If use cannot be avoided, monitor serum sodium and potassium concentrations. (5.3, 5.4, 5.5, 8.4)
- Fluid Overload: Avoid in patients with or at risk for fluid and/or solute overloading. If use cannot be avoided, monitor daily fluid balance and electrolyte, concentrations and acid-base balance, as needed and especially during prolonged use. (5.6)
- Refeeding Syndrome: Monitor severely undernourished patients and slowly increase nutrient intake. (5.7)

6 ADVERSE REACTIONS

Adverse reactions include electrolyte imbalances, hyperglycemia, and hypervolemia and injection site reactions. (6)

To report SUSPECTED ADVERSE REACTIONS, contact Baxter Healthcare at 1-866-888-2472 or FDA at 1-800-FDA-1088 or www.fda.gov/medwatch.

7 DRUG INTERACTIONS

- Other Products that Affect Glycemic Control, Vasopressin or Fluid and/or Electrolyte Balance: Monitor blood glucose concentrations, fluid balance serum electrolyte concentrations and acid-base balance. (7.1)
- Lithium: Decreased lithium concentrations with concomitant use; monitor serum lithium concentrations. (7.2)

FULL PRESCRIBING INFORMATION

1 INDICATIONS AND USAGE

Dextrose and Sodium Chloride Injection is indicated as a source of water, electrolytes and calories.

2 DOSAGE AND ADMINISTRATION

2.1 Important Administration Instructions

- Dextrose and Sodium Chloride Injection is only for intravenous infusion.
- The osmolarity of Dextrose and Sodium Chloride Injection, ranges from 280 to 560 mOsmol/L (calc). Peripheral administration is generally acceptable; however; consider central vein administration if there is peripheral vein irritation, phlebitis, and/or associated pain.
- Do not administer Dextrose and Sodium Chloride Injection simultaneously with blood products through the same administration set because of the possibility of pseudoagglutination or hemolysis.
- To prevent air embolism, use a non-vented infusion set or close the vent on a vented set, avoid multiple connections, do not connect flexible containers in series, fully evacuate residual gas in the container prior to administration, do not pressurize the flexible container to increase flow rates, and if administration is controlled by a pumping device, turn off pump before the container runs dry.
- Prior to infusion, visually inspect the solution for particulate matter. The solution should be clear and there should be no precipitates. Do not administer unless solution is clear and container is undamaged.
- Use of a final filter is recommended during administration of parenteral solutions, where possible.

2.2 Recommended Dosage

The choice of the specific, sodium chloride, and dextrose concentrations, rate and volume depends on the age, weight, clinical and metabolic conditions of the patient and concomitant therapy. Electrolyte supplementation may be indicated according to the clinical needs of the patient.

The administration rate should be governed, especially for premature infants with low birth weight, during the first few days of therapy, by the patient’s tolerance to dextrose. Increase the infusion rate gradually as indicated by frequent monitoring of blood glucose concentrations [see Warnings and Precautions (5.2), Use in Specific Populations (8.4)].

2.3 Instructions for Use

To Open

- Do not remove container from overwrap until ready to use.
- Tear overwrap down side at slit and remove solution container.
- Visually inspect the container. Some opacity of the plastic due to moisture absorption during the sterilization process may be observed. This is normal and does not affect the solution quality or safety. The opacity will diminish gradually. Evaluate the following:
  ∘ If the outlet port protector is damaged, detached, or not present, discard container.
  ∘ Check to ensure the solution is clear and there are no precipitates. Discard if there is a color change and/or the appearance of precipitates, insoluble complexes or crystals.
  ∘ Check for minute leaks by squeezing inner bag firmly. If leaks are found, discard container.

Preparation for Administration

1. Suspend container from eyelet support.
2. Remove protector from outlet port at bottom of container.
3. Attach administration set. Refer to complete directions accompanying set.

To Add Medication

- Additives may be incompatible. Complete information is not available. Do not use additives known or determined to be incompatible.
- Consult with pharmacist, if available. If, in the informed judgment of the healthcare provider, it is deemed advisable to introduce additives, use aseptic technique.
- When introducing additives, consult the instructions for use of the medication to be added and other relevant literature.
- Before adding a substance or medication, verify that it is soluble and/or stable in Dextrose and Sodium Chloride Injection and that the pH range of Dextrose and Sodium Chloride Injection is appropriate.

To Add Medication Before Solution Administration

1. Prepare medication site.
2. Using syringe with 19 to 22-gauge needle, puncture resealable medication port and inject.
3. Mix solution and medication thoroughly. For high density medication such as potassium chloride, squeeze ports while ports are upright and mix thoroughly.
4. After addition, check to ensure the solution is clear and there are no precipitates. Discard if there is a color change and/or the appearance of precipitates, insoluble complexes or crystals.

To Add Medication During Solution Administration

1. Close clamp on the set.
2. Prepare medication site.
3. Using syringe with 19 to 22-gauge needle, puncture resealable medication port and inject.
4. Remove container from IV pole and/or turn to an upright position.
5. Evacuate both ports by squeezing them while container is in the upright position.
6. Mix solution and medication thoroughly.
7. After addition, check to ensure the solution is clear and there are no precipitates. Discard if there is a color change and/or the appearance of precipitates, insoluble complexes or crystals, do not use.
8. Return container to in use position and continue with administration.

Storage

- Use promptly; do not store solutions containing additives.
- Single-dose container.
- Discard any unused portion.

3 DOSAGE FORMS AND STRENGTHS

Dextrose and Sodium Chloride Injection are clear solutions in 250 mL, 500 mL and 1000 mL single-dose, flexible containers:

250 mL flexible container

- 5% Dextrose and 0.2% Sodium Chloride Injection, USP

500 mL flexible container

- 5% Dextrose and 0.45% Sodium Chloride Injection, USP
- 5% Dextrose and 0.9% Sodium Chloride Injection, USP

1000 mL flexible container

- 2.5% Dextrose and 0.45% Sodium Chloride Injection, USP
- 5% Dextrose and 0.2% Sodium Chloride Injection, USP
- 5% Dextrose and 0.45% Sodium Chloride Injection, USP
- 5% Dextrose and 0.9% Sodium Chloride Injection, USP

4 CONTRAINDICATIONS

Dextrose and Sodium Chloride Injection is contraindicated in patients with:

- known hypersensitivity to dextrose and/or sodium chloride [see Warnings and Precautions 5.1)]
- clinically significant hyperglycemia [see Warnings and Precautions (5.2)]

5 WARNINGS AND PRECAUTIONS

5.1 Hypersensitivity Reactions

Hypersensitivity and infusion reactions, including anaphylaxis, have been reported with Dextrose and Sodium Chloride Injection [see Adverse Reactions (6)]. Stop the infusion immediately if signs or symptoms of a hypersensitivity or infusion reaction develops [see Contraindications (4)]. Appropriate therapeutic countermeasures must be instituted as clinically indicated.

5.2 Hyperglycemia and Hyperosmolar Hyperglycemic State

The use of dextrose infusions in patients with impaired glucose tolerance may worsen hyperglycemia. Administration of dextrose at a rate exceeding the patient’s utilization rate may lead to hyperglycemia, coma, and death.

Hyperglycemia is associated with an increase in serum osmolality, resulting in osmotic diuresis, dehydration and electrolyte losses. Patients with underlying central nervous system disease and renal impairment who receive dextrose infusions, may be at greater risk of developing hyperosmolar hyperglycemic state.

Monitor blood glucose concentrations and treat hyperglycemia to maintain concentrations within normal limits while administering Dextrose and Sodium Chloride Injection. Insulin may be administered or adjusted to maintain optimal blood glucose concentrations.

5.3 Hyponatremia

Dextrose and Sodium Chloride Injection is a hypertonic solution [see Description, Table 1 (11)]. In the body, however, glucose containing fluids can become extremely physiologically hypotonic due to rapid glucose metabolization. Monitoring of serum sodium is particularly important for hypotonic fluids.

Depending on the tonicity of the solution, the volume and rate of infusion, and depending on a patient’s underlying clinical condition and capability to metabolize glucose, intravenous administration of glucose can cause electrolyte disturbances, most importantly hypo- or hyperosmotic hyponatremia.

The risk for hyponatremia is increased, in pediatric patients, elderly patients, postoperative patients, those with psychogenic polydipsia and in patients treated with medications that increase the risk of hyponatremia (such as certain diuretic, antiepileptic and psychotropic medications) [see Drug Interactions (7.1)].

Acute hyponatremia can lead to acute hyponatremic encephalopathy characterized by headache, nausea, seizures, lethargy and vomiting. Patients with brain edema are at particular risk of severe, irreversible and life-threatening brain injury. Patients at increased risk for developing complications of hyponatremia, such as hyponatremic encephalopathy include pediatric patients; women, in particular, premenopausal women; patients with hypoxemia; and in patients with underlying central nervous system disease [see Use in Specific Populations (8.4, 8.5)].

Avoid Dextrose and Sodium Chloride Injection in patients with or at risk for hyponatremia. If use cannot be avoided, monitor serum sodium concentrations.

Rapid correction of hyponatremia is potentially dangerous with risk of serious neurologic complications such as osmotic demyelination syndrome with risk of seizures and cerebral edema. To avoid complications, monitor serum sodium and chloride concentrations, fluid status, acid-base balance, and signs of neurologic complications.

High volume infusion must be used with close monitoring in patients with cardiac or pulmonary failure, and in patients with non-osmotic vasopressin release (including SIADH), due to the risk of hospital-acquired hyponatremia.

5.4 Hypokalemia

Excessive administration of Dextrose and Sodium Chloride Injection may result in significant hypokalemia. Hypokalemic periodic paralysis, metabolic alkalosis, increased gastrointestinal losses (e.g. diarrhea, vomiting), prolonged low potassium diet, or primary hyperaldosteronism may increase the risk of hypokalemia. Avoid the administration of Dextrose and Sodium Chloride Injection in patients with or at risk of hypokalemia or taking medications that may increase the risk. If use cannot be avoided, monitor serum potassium levels.

5.5 Hypernatremia and Hyperchloremia

Electrolyte imbalances such as hypernatremia and hyperchloremia, leading to metabolic acidosis may occur with solutions containing 0.9% sodium chloride.

Conditions that may increase the risk of hypernatremia, fluid overload and edema (central and peripheral), include patients with pre-eclampsia, primary hyperaldosteronism and secondary hyperaldosteronism associated with, for example, hypertension, congestive heart failure, severe renal impairment, liver disease (including cirrhosis), and renal disease (including renal artery stenosis, nephrosclerosis).

Medications such as corticosteroids or corticotropin, may increase the risk of sodium and fluid retention.

Avoid in patients with or at risk for hypernatremia. If use cannot be avoided, monitor serum sodium concentrations.

Rapid correction of hypernatremia is potentially dangerous with risk of serious neurologic complications. Excessively rapid correction of hypernatremia is also associated with a risk for serious neurologic complications such as osmotic demyelination syndrome (ODS) with risk of seizures and cerebral edema.

5.6 Fluid Overload

Depending on the volume and rate of infusion, the patient’s underlying clinical condition and capability to metabolize dextrose, intravenous administration of Dextrose and Sodium Chloride Injection can cause fluid and/or solute overloading resulting in dilution of serum electrolyte concentrations, overhydration, congested states or pulmonary edema.

Avoid Dextrose and Sodium Chloride Injection in patients with or at risk for fluid and/or solute overloading. If use cannot be avoided, monitor fluid balance, electrolyte concentrations, and acid-base balance as needed and especially during prolonged use.

5.7 Refeeding Syndrome

Refeeding severely undernourished patients may result in the refeeding syndrome that is characterized by the shift of potassium, phosphorus, and magnesium intracellularly as the patient becomes anabolic. Thiamine deficiency and fluid retention may also develop. To prevent these complications, monitor severely undernourished patients and slowly increasing nutrient intake.

6 ADVERSE REACTIONS

- Anaphylactic reaction, hypersensitivity, and chills

- Hyponatremia (applies to solutions containing less than 0.9% Sodium Chloride)

Reactions which may occur because of the solution or the technique of administration include febrile response, infection at the site of injection, venous thrombosis or phlebitis extending from the site of injection, extravasation and hypervolemia.

If an adverse reaction does occur, discontinue the infusion, evaluate the patient, institute appropriate therapeutic countermeasures and save the remainder of the fluid for examination if deemed necessary.

7 DRUG INTERACTIONS

7.1 Other Products that Affect Glycemic Control, Vasopressin or Fluid and/or Electrolyte Balance

Dextrose and Sodium Chloride Injection can affect glycemic control, vasopressin and fluid and/or electrolyte balance [see Warnings and Precautions (5.2, 5.3, 5.4, 5.5, 5.6)]. Monitor blood glucose concentrations, fluid balance, serum electrolyte concentrations and acid-base balance when using Dextrose and Sodium Chloride Injection in patients treated with other substances that affect glycemic control, vasopressin or fluid and/or electrolyte balance.

7.2 Lithium

Renal sodium and lithium clearance may be increased during administration of Dextrose and Sodium Chloride Injection resulting in decreased serum lithium concentrations. Monitor serum lithium concentrations during concomitant use.

8 USE IN SPECIFIC POPULATIONS

8.1 Pregnancy

Risk Summary

Appropriate administration of Dextrose and Sodium Chloride Injection during pregnancy is not expected to cause adverse developmental outcomes, including congenital malformations. Animal reproduction studies have not been conducted with Dextrose and Sodium Chloride Injection.

The estimated background risk of major birth defects and miscarriage for the indicated population is unknown. All pregnancies have a background risk of birth defect, loss, or other adverse outcomes. In the U.S. general population, the estimated background risk of major birth defects and miscarriage in clinically recognized pregnancies is 2 to 4% and 15 to 20%, respectively.

8.2 Lactation

Risk Summary

Sodium is present in human breast milk. There are no data on the effects of Dextrose and Sodium Chloride Injection on a breastfed infant or the effects on milk production.

The developmental and health benefits of breastfeeding should be considered along with the mother’s clinical need for Dextrose and Sodium Chloride Injection and any potential adverse effects on the breastfed infant from Dextrose and Sodium Chloride Injection or from the underlying maternal condition.

8.4 Pediatric Use

The safety profile of Dextrose and Sodium Chloride Injection in pediatric patients is similar to adults.

Neonates, especially premature infants with low birth weight, are at increased risk of developing hypo- or hyperglycemia and therefore need close monitoring during treatment with intravenous glucose solutions to ensure adequate glycemic control in order to avoid potential long-term adverse effects.

Closely monitor plasma electrolyte concentrations in pediatric patients who may have impaired ability to regulate fluids and electrolytes. In very low birth weight infants, excessive or rapid administration of Dextrose and Sodium Chloride Injection may result in increased serum osmolality and risk of intracerebral hemorrhage.

Children (including neonates and older children) are at increased risk of developing hyponatremia as well as for developing hyponatremic encephalopathy.

8.5 Geriatric Use

Clinical studies of Dextrose and Sodium Chloride Injection did not include sufficient numbers of subjects aged 65 and over to determine whether they respond differently from younger subjects.

Elderly patients are at increased risk of developing hyponatremia as well as for developing hyponatremic encephalopathy [see Warnings and Precautions (5.3)]. Dextrose and Sodium Chloride Injection is known to be substantially excreted by the kidney, and the risk of adverse reactions to this product may be greater in patients with impaired renal function [see Warnings and Precautions (5.2, 5.5)].

Dose selection for an elderly patient should be cautious, starting at the low end of the dosing range, reflecting the greater frequency of decreased hepatic, renal, or cardiac function, and of concomitant disease or other drug therapy.

8.6 Renal Impairment

Administration of Dextrose and Sodium Chloride Injection in patients with renal impairment may result in hyperosmolar hyperglycemic state, hyponatremia, and/or fluid overload. Monitor patients with renal impairment for development of these adverse reactions [see Warnings and Precautions (5.2, 5.3, 5.5, 5.6)].

10 OVERDOSAGE

Excessive administration of Dextrose and Sodium Chloride Injection can cause:

Electrolyte and Fluid Disorders

- Hyperglycemia, hyperosmolality, and adverse effects on water and electrolyte balance, and corresponding complications, which can be fatal [see Warnings and Precautions (5.2)].
- Hyponatremia, manifestations may include seizures, coma, cerebral edema and death) [see Warnings and Precautions (5.3)].
- Hypernatremia, especially in patients with severe renal impairment [see Warnings and Precautions (5.5)].
- Fluid overload (which can lead to central and/or peripheral edema) [see Warnings and Precautions (5.6)].

When assessing an overdose, any additives in the solution must also be considered. Clinically significant overdose of Dextrose and Sodium Chloride Injection may, therefore, constitute a medical emergency. The effects of an overdose may require immediate medical attention and treatment.

Interventions include discontinuation of the infusion, dose reduction, monitoring of fluid balance, electrolyte concentrations and acid-base balance and institution of appropriate corrective measures such as administration of exogenous insulin.

11 DESCRIPTION

Dextrose and Sodium Chloride Injection, USP is a sterile, nonpyrogenic solution for fluid and electrolyte replenishment and caloric supply in single-dose containers for intravenous administration. It contains no antimicrobial agents. Composition, osmolarity, pH, ionic concentration and caloric content are shown in Table 1.

Table 1.
 | Size (mL) | Composition (g/L) |  | [Normal physiologic osmolarity range is approximately 280 to 310 mOsmol/L.] Osmolarity (mOsmol/L) (calc.) | pH | Ionic Concentration (mEq/L) |  | Caloric Content (kcal/L)
 | Size (mL) | **Dextrose Hydrous, USP | Sodium Chloride, USP (NaCl) | [Normal physiologic osmolarity range is approximately 280 to 310 mOsmol/L.] Osmolarity (mOsmol/L) (calc.) | pH | Sodium | Chloride
2.5% Dextrose and 0.45% Sodium Chloride Injection, USP | 1000 | 25 | 4.5 | 280 | 4.5; (3.2 to 6.5) | 77 | 77 | 85
5% Dextrose and 0.2% Sodium Chloride Injection, USP | 250; 1000 | 50 | 2 | 321 | 4.0; (3.2 to 6.5) | 34 | 34 | 170
5% Dextrose and 0.33% Sodium Chloride Injection, USP | 250; 1000 | 50 | 3.3 | 365 | 4.0; (3.2 to 6.5) | 56 | 56 | 170
5% Dextrose and 0.45% Sodium Chloride Injection, USP | 500; 1000 | 50 | 4.5 | 406 | 4.0; (3.2 to 6.5) | 77 | 77 | 170
5% Dextrose and 0.9% Sodium Chloride Injection, USP | 500; 1000 | 50 | 9 | 560 | 4.0; (3.2 to 6.5) | 154 | 154 | 170

Dextrose is derived from corn.

The VIAFLEX Plus plastic container is fabricated from a specially formulated polyvinyl chloride (PL 146 Plastic). The amount of water that can permeate from inside the container into the overwrap is insufficient to affect the solution significantly. Solutions in contact with the plastic container can leach out certain of its chemical components in very small amounts within the expiration period, e.g., di-2-ethylhexyl phthalate (DEHP), up to 5 parts per million. However, the safety of the plastic has been confirmed in tests in animals according to USP biological tests for plastic containers as well as by tissue culture toxicity studies.

12 CLINICAL PHARMACOLOGY

Dextrose and Sodium Chloride Injection, USP has value as a source of water, electrolytes, and calories. It is capable of inducing diuresis depending on the clinical condition of the patient.

12.1 Mechanism of Action

Dextrose and Sodium Chloride Injection is a source of water, electrolytes and calories. It is capable of inducing diuresis depending on the clinical condition of the patient.

16 HOW SUPPLIED/STORAGE AND HANDLING

Dextrose and Sodium Chloride Injection are clear solutions in 250 mL, 500 mL and 1000 mL single-dose, flexible containers available as follows:

Code | Size (mL) | NDC | Product Name
2B1024 | 1000 | 0338-0073-04 | 2.5% Dextrose and 0.45% Sodium Chloride Injection, USP
2B1092 | 250 | 0338-0077-02 | 5% Dextrose and 0.2% Sodium Chloride Injection, USP
2B1094 | 1000 | 0338-0077-04 | 5% Dextrose and 0.2% Sodium Chloride Injection, USP
2B1073 | 500 | 0338-0085-03 | 5% Dextrose and 0.45% Sodium Chloride Injection, USP
2B1074 | 1000 | 0338-0085-04 | 5% Dextrose and 0.45% Sodium Chloride Injection, USP
2B1063 | 500 | 0338-0089-03 | 5% Dextrose and 0.9% Sodium Chloride Injection, USP
2B1064 | 1000 | 0338-0089-04 | 5% Dextrose and 0.9% Sodium Chloride Injection, USP

Storage: Avoid excessive heat. Store at room temperature (25°C/77°F); brief exposure up to 40°C/104°F does not adversely affect the product.

17 PATIENT COUNSELING INFORMATION

Inform patients, caregivers or home healthcare providers of the following risks of Dextrose and Sodium Chloride Injection:

- Hypersensitivity reactions [see Warnings and Precautions (5.1)]
- Hyperglycemia and hyperosmolar hyperglycemic state [see Warnings and Precautions (5.2)]
- Hyponatremia [see Warnings and Precautions (5.3)]
- Hypokalemia [see Warnings and Precautions (5.4)]
- Hypernatremia and hyperchloremia [see Warnings and Precautions (5.5)]
- Fluid overload [see Warnings and Precautions (5.6)]
- Refeeding syndrome [see Warnings and Precautions (5.7)]

Baxter Healthcare Corporation
Deerfield, IL 60015 USA
Printed in USA

Distributed in Canada by
Baxter Corporation
Mississauga, ON L5N 0C2

07-19-00-9764

Baxter, and Viaflex and PL 146 are trademarks of Baxter International Inc.

For Product Information
1-800-933-0303

PACKAGE/LABEL PRINCIPAL DISPLAY PANEL

Container Label

Container Label

LOT EXP

2B1063
NDC 0338-0089-03

5% Dextrose and
0.9% Sodium Chloride
Injection USP

500 mL EACH 100 mL CONTAINS 5 g DEXTROSE HYDROUS USP
900 mg SODIUM CHLORIDE USP pH 4.0 (3.2 TO 6.5)
mEq/L SODIUM 154 CHLORIDE 154 HYPERTONIC
OSMOLARITY 560 mOsmol/L (CALC) STERILE
NONPYROGENIC SINGLE DOSE CONTAINER ADDITIVES MAY BE
INCOMPATIBLE CONSULT WITH PHARMACIST IF AVAILABLE
WHEN INTRODUCING ADDITIVES USE ASEPTIC TECHNIQUE MIX
THOROUGHLY DO NOT STORE DOSAGE INTRAVENOUSLY AS
DIRECTED BY A PHYSICIAN SEE DIRECTIONS CAUTIONS
SQUEEZE AND INSPECT INNER BAG WHICH MAINTAINS PRODUCT
STERILITY DISCARD IF LEAKS ARE FOUND MUST NOT BE USED
IN SERIES CONNECTIONS DO NOT USE UNLESS SOLUTION IS
CLEAR RX ONLY STORE UNIT IN MOISTURE BARRIER
OVERWRAP AT ROOM TEMPERATURE (25°C/77°F) UNTIL READY
TO USE AVOID EXCESSIVE HEAT SEE INSERT

VIAFLEX CONTAINER PL 146 PLASTIC

BAXTER VIAFLEX AND PL 146 ARE TRADEMARKS OF
BAXTER INTERNATIONAL INC

FOR PRODUCT INFORMATION 1-800-933-0303

BAXTER Logo
BAXTER HEALTHCARE CORPORATION
DEERFIELD IL 60015 USA

MADE IN USA

1

2

3

4

Container Label

Container Label

LOT EXP

2B1024
NDC 0338-0073-04

2.5% Dextrose
and 0.45%
Sodium Chloride
Injection USP

1000 mL

EACH 100 mL CONTAINS 2.5 g DEXTROSE HYDROUS USP
450 mg SODIUM CHLORIDE USP pH 4.0 (3.2 TO 6.5)
mEq/L SODIUM 77 CHLORIDE 77 OSMOLARITY 280
mOsmol/L (CALC) STERILE NONPYROGENIC SINGLE
DOSE CONTAINER ADDITIVES MAY BE INCOMPATIBLE
CONSULT WITH PHARMACIST IF AVAILABLE WHEN
INTRODUCING ADDITIVES USE ASEPTIC TECHNIQUE MIX
THOROUGHLY DO NOT STORE DOSAGE INTRAVENOUSLY
AS DIRECTED BY A PHYSICIAN SEE DIRECTIONS CAUTIONS
SQUEEZE AND INSPECT INNER BAG WHICH MAINTAINS
PRODUCT STERILITY DISCARD IF LEAKS ARE FOUND MUST
NOT BE USED IN SERIES CONNECTIONS DO NOT USE UNLESS
SOLUTION IS CLEAR RX ONLY STORE UNIT IN MOISTURE
BARRIER OVERWRAP AT ROOM TEMPERATURE (25°C/77°F)
UNTIL READY TO USE AVOID EXCESSIVE HEAT SEE INSERT

VIAFLEX CONTAINER PL 146 PLASTIC

BAXTER VIAFLEX AND PL 146 ARE TRADEMARKS OF
BAXTER INTERNATIONAL INC

FOR PRODUCT INFORMATION 1-800-933-0303

Baxter Logo
BAXTER HEALTHCARE CORPORATION
DEERFIELD IL 60015 USA
MADE IN USA

1

2

3

4

5

6

7

8

9

Container Label

Container Label

LOT EXP

2B1092
NDC 0338-0077-02

5% Dextrose and
0.2% Sodium Chloride
Injection USP

250 mL EACH 100 mL CONTAINS
5 g DEXTROSE HYDROUS
USP 200 mg SODIUM CHLORIDE USP
pH 4.0 (3.2 TO 6.5) mEq/L SODIUM 34
CHLORIDE 34 OSMOLARITY 321 mOsmol/L
(CALC) STERILE NONPYROGENIC SINGLE
DOSE CONTAINER ADDITIVES MAY BE
INCOMPATIBLE CONSULT WITH PHARMACIST
IF AVAILABLE WHEN INTRODUCING ADDITIVES
USE ASEPTIC TECHNIQUE MIX THOROUGHLY
DO NOT STORE DOSAGE INTRAVENOUSLY AS
DIRECTED BY A PHYSICIAN SEE DIRECTIONS
CAUTIONS SQUEEZE AND INSPECT INNER
BAG WHICH MAINTAINS PRODUCT STERILITY
DISCARD IF LEAKS ARE FOUND MUST NOT BE
USED IN SERIES CONNECTIONS DO NOT
USE UNLESS SOLUTION IS CLEAR RX
ONLY STORE UNIT IN MOISTURE BARRIER
OVERWRAP AT ROOM TEMPERATURE
(25°C/77°F) UNTIL READY TO USE AVOID
EXCESSIVE HEAT SEE INSERT

VIAFLEX CONTAINER PL 146 PLASTIC

BAXTER VIAFLEX AND PL 146 ARE
TRADEMARKS OF BAXTER INTERNATIONAL INC

FOR PRODUCT INFORMATION
1-800-933-0303

BAXTER Logo
BAXTER HEALTHCARE CORPORATION
DEERFIELD IL 60015 USA
MADE IN USA

50

100

150

200

Container Label

Container Label

LOT EXP

2B1073
NDC 0338-0085-03

5% Dextrose and
0.45% Sodium Chloride
Injection USP

500 mL

EACH 100 mL CONTAINS 5 g DEXTROSE HYDROUS USP
450 mg SODIUM CHLORIDE USP pH 4.0 (3.2 TO 6.5)
mEq/L SODIUM 77 CHLORIDE 77 HYPERTONIC OSMOLARITY
406 mOsmol/L (CALC) STERILE NONPYROGENIC SINGLE
DOSE CONTAINER ADDITIVES MAY BE INCOMPATIBLE CONSULT
WITH PHARMACIST IF AVAILABLE WHEN INTRODUCING ADDITIVES
USE ASEPTIC TECHNIQUE MIX THOROUGHLY DO NOT STORE
DOSAGE INTRAVENOUSLY AS DIRECTED BY A PHYSICIAN SEE
DIRECTIONS CAUTIONS SQUEEZE AND INSPECT INNER BAG
WHICH MAINTAINS PRODUCT STERILITY DISCARD IF LEAKS ARE
FOUND MUST NOT BE USED IN SERIES CONNECTIONS DO NOT
USE UNLESS SOLUTION IS CLEAR RX ONLY STORE UNIT IN
MOISTURE BARRIER OVERWRAP AT ROOM TEMPERATURE
(25°C/77°F) UNTIL READY TO USE AVOID EXCESSIVE HEAT
SEE INSERT

VIAFLEX CONTAINER PL 146 PLASTIC

BAXTER VIAFLEX AND PL 146 ARE
TRADEMARKS OF BAXTER INTERNATIONAL INC

FOR PRODUCT INFORMATION 1-800-933-0303

BAXTER Logo
BAXTER HEALTHCARE CORPORATION
DEERFIELD IL 60015 USA

MADE IN USA

1

2

3

4